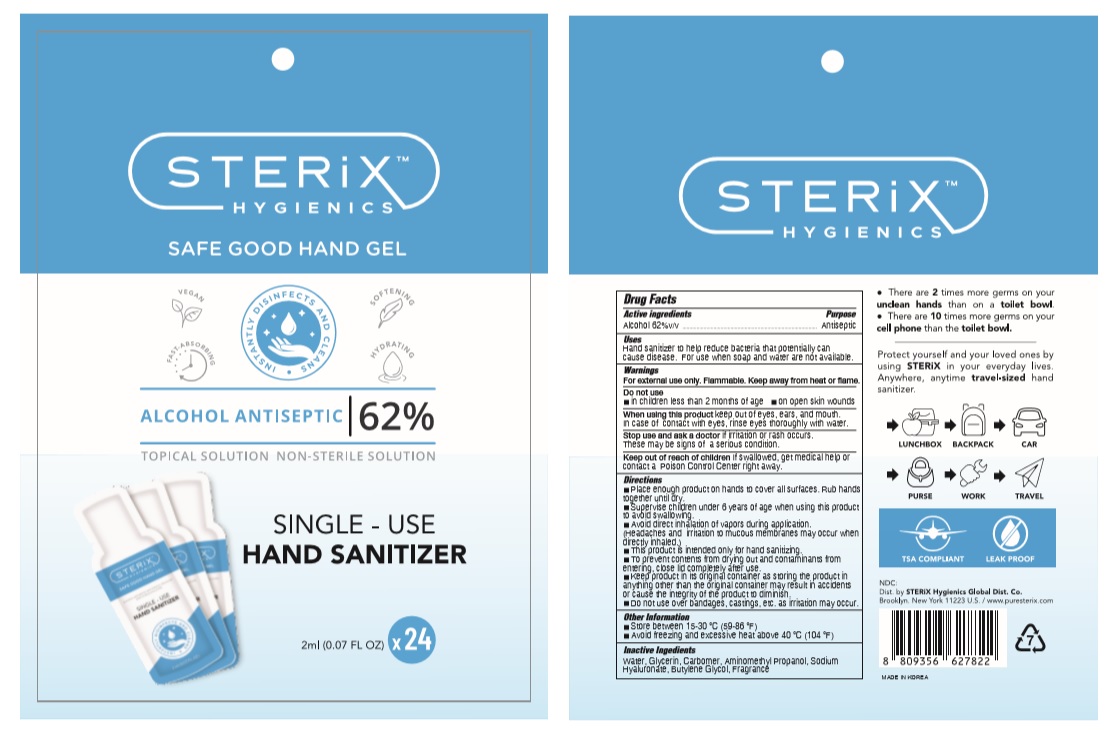 DRUG LABEL: STERIX SAFE GOOD HAND Gel
NDC: 74339-0224 | Form: GEL
Manufacturer: PL COSMETIC
Category: otc | Type: HUMAN OTC DRUG LABEL
Date: 20200512

ACTIVE INGREDIENTS: ALCOHOL 1.24 mL/2 mL
INACTIVE INGREDIENTS: GLYCERIN; CARBOMER HOMOPOLYMER, UNSPECIFIED TYPE; WATER; BUTYLENE GLYCOL; HYALURONATE SODIUM; AMINOMETHYLPROPANOL

STERIX SAFE GOOD HAND Gel 2 ml x 24 EA 74339-0224-2